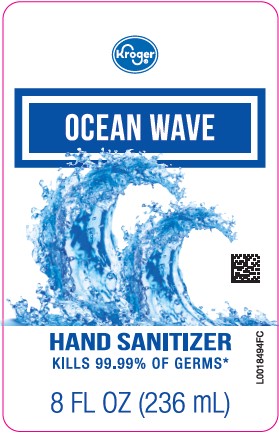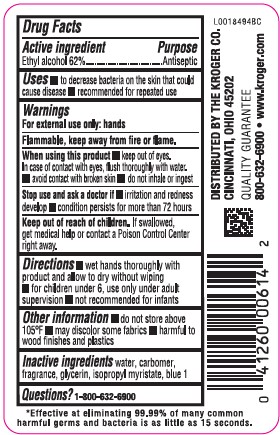 DRUG LABEL: Alcohol
NDC: 59450-471 | Form: LIQUID
Manufacturer: The Kroger Co.
Category: otc | Type: HUMAN OTC DRUG LABEL
Date: 20260227

ACTIVE INGREDIENTS: ALCOHOL 62 mL/100 mL
INACTIVE INGREDIENTS: WATER; CARBOXYPOLYMETHYLENE; GLYCERIN; ISOPROPYL MYRISTATE; FD&C BLUE NO. 1

Kroger 471.000/471AA
Ocean Breeze Hand Sanitizer

Active ingredient

Ethyl Alcohol 62%

Purpose

Antiseptic

Uses

- to decrease bacteria on the skin that could cause disease
- recommended for repeated use

Warnings

For exterenal use only: hands

Flammable, keep away from fire or flame.

When using this product

- keep out of eyes. In case of contact with eyes, flush thoroughly with water.
- avoid contact with broken skin
- do not inhale or ingest

Stop use and ask a doctor if

- irritation and redness develop
- condition persists for more than 72 hours

Keep out of reach of children.

If swallowed, get medical help or contact a Poison Control Center right away.

Directions

- wet hands thoroughly with product and allow to dry without wiping
- for children under 6, use only under adult supervision
- not recommended for infants

Other information

- do not store above 105⁰F
- may discolor some fabrics
- harmful to wood finishes and plastics

Inactive ingredients

water, carbomer, fragrance, glycerin, isopropyl myristate, blue 1

Questions?

1-800-632-6900

Claims

*Effective at eliminating 99.99% of many common harmful germs and bacteria in as little as 15 seconds.

ADVERSE REACTION

Distributed by The Kroger Co.

Cincinnati, Ohio 45202

Quality guarantee

800-632-6900 www.kroger.com

Principal display panel

Kroger®

Ocean Wave

Hand Sanitizer

kills 99.99% of germs*

8 FL OZ (236 mL)